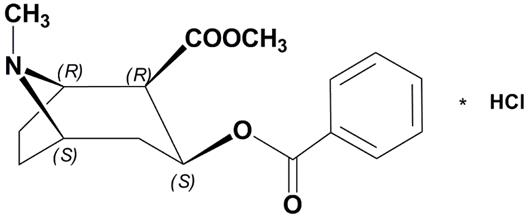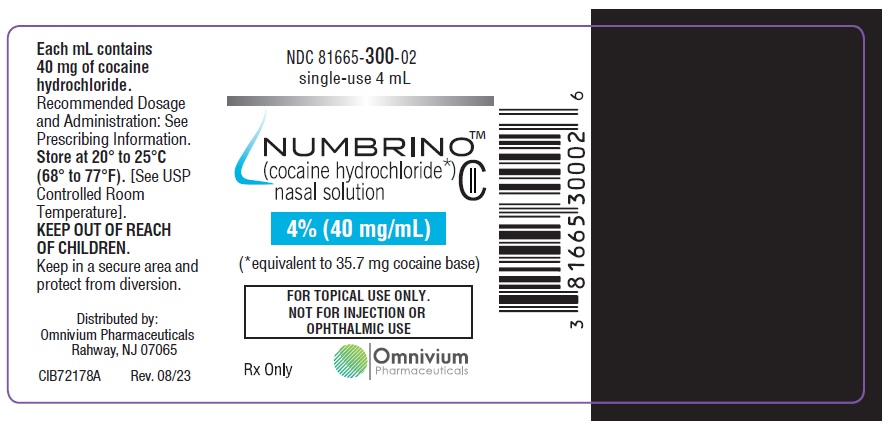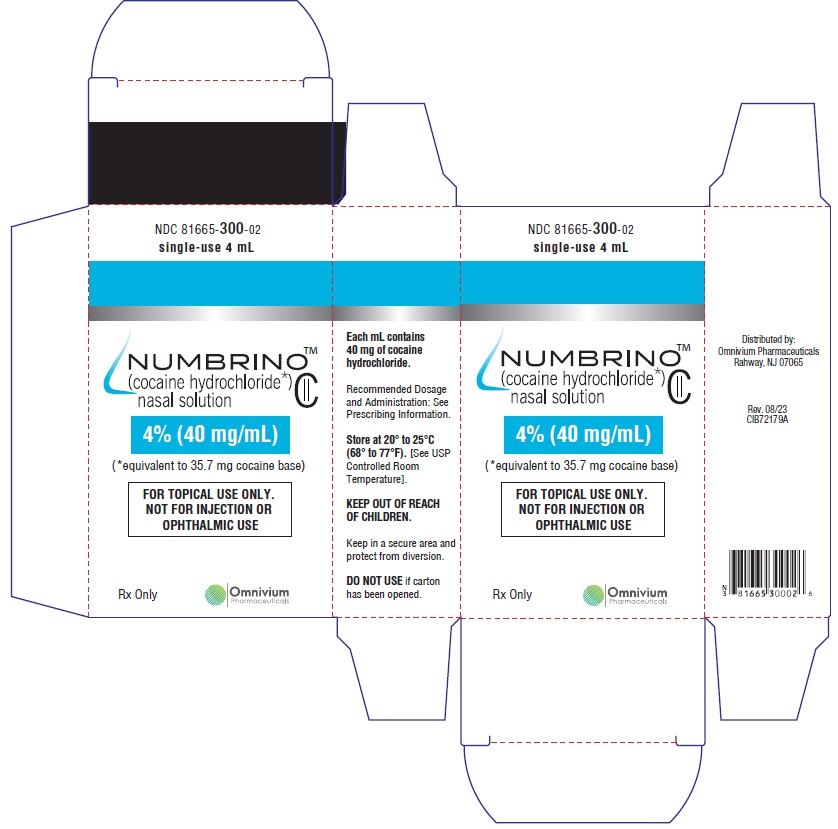 DRUG LABEL: NUMBRINO
NDC: 81665-300 | Form: SOLUTION
Manufacturer: OMNIVIUM PHARMACEUTICALS LLC.
Category: prescription | Type: HUMAN PRESCRIPTION DRUG LABEL
Date: 20260112
DEA Schedule: CII

ACTIVE INGREDIENTS: COCAINE HYDROCHLORIDE 40 mg/1 mL
INACTIVE INGREDIENTS: CITRIC ACID MONOHYDRATE; SODIUM BENZOATE; D&C YELLOW NO. 10; FD&C GREEN NO. 3; WATER

HIGHLIGHTS OF PRESCRIBING INFORMATION

These highlights do not include all the information needed to use NUMBRINO safely and effectively. See full prescribing information for NUMBRINO.
NUMBRINOTM (cocaine hydrochloride) nasal solution, CII
Initial U.S. Approval: 2017

WARNING: ABUSE AND DEPENDENCE

See full prescribing information for complete boxed warning.

CNS stimulants, including cocaine hydrochloride, have a high potential for abuse and dependence. (5.1)

1 INDICATIONS AND USAGE

NUMBRINO (cocaine hydrochloride) nasal solution is an ester local anesthetic indicated for the introduction of local anesthesia of the mucous membranes for diagnostic procedures and surgeries on or through the nasal cavities of adults. (1)

2 DOSAGE AND ADMINISTRATION

- For intranasal use only. (2.1)
- Do not apply to damaged nasal mucosa. (2.1)
- NUMBRINO should not be substituted for other nasal cocaine products unless determined by FDA to be substitutable. (2.1)
- The recommended dose of NUMBRINO ranges from 40 mg to 160 mg, depending on the nasal surface area to be anesthetized and the procedure to be performed. (2.2)
  NUMBRINO should be administered by means of cotton or rayon applicator pledgets applied to the nasal mucosa. (2)

- One pledget will absorb one mL of NUMBRINO nasal solution. (2.2)
- Preparation and Application:
  - Draw up 4 mL NUMBRINO 4% nasal solution into a syringe calibrated in mL. Apply 2 mL NUMBRINO nasal solution to the top of four stacked pledgets. Turn the stacked pledgets over and apply 2 mL NUMBRINO nasal solution to the other side. (2.3)
  - NUMBRINO nasal solution should be evenly distributed on all pledgets. (2.3)
  - Following soaking, place a maximum of two pledgets in each nasal cavity. (2.3)

Leave pledgets in place for up to 20 minutes. (2.3)

Pledgets should be removed immediately upon any sign or symptom of an adverse event. (2.2)

3 DOSAGE FORMS AND STRENGTHS

Nasal solution:

- 4% nasal solution (40 mg/ mL; available in both 4mL and 10mL bottles) (3)

4 CONTRAINDICATIONS

- Hypersensitivity to cocaine, or any component of NUMBRINO. (4)

5 WARNINGS AND PRECAUTIONS

- NUMBRINO is for TOPICAL USE ONLY. NOT FOR INJECTION OR OPHTHALMIC USE. (5)
- Seizures: NUMBRINO may lower the convulsive threshold. Monitor patients for development of seizures.
- Blood Pressure and Heart Rate Increases: Monitor vital signs, including heart rate and rhythm, in patients after receiving NUMBRINO. Avoid use of NUMBRINO in patients with a recent or active history of myocardial infarction, coronary artery disease, congestive heart failure, irregular heart rhythm, abnormal ECG, uncontrolled hypertension, or thyrotoxicosis.

6 ADVERSE REACTIONS

The most common adverse reactions (> 1%) occurring in patients treated with NUMBRINO were hypertension, tachycardia, and sinus tachycardia. (6.1)

To report SUSPECTED ADVERSE REACTIONS, contact Omnivium Pharmaceuticals LLC at 1-888-807-1048 or FDA at 1-800-FDA-1088 or www.fda.gov/medwatch.

7 DRUG INTERACTIONS

- Epinephrine, Phenylephrine: There have been reports of myocardial ischemia, myocardial infarction, and ventricular arrhythmias with concomitant use during nasal surgery. Avoid use of additional vasoconstrictor agents with NUMBRINO. If concomitant use is unavoidable, prolonged vital sign and ECG monitoring may be required. (5.3, 7.2)
- Disulfiram: Disulfiram treatment increases plasma cocaine exposure. Avoid using NUMBRINO in patients taking disulfiram. (7.3)
- CNS stimulants: Concomitant administration may result in nervousness, irritability, or possibly convulsions. (7.1)
- Cholinesterase inhibitors: Concomitant administration may increase the risk of cocaine toxicity. (7.4)
- Sympathomimetics, postganglionic blocking agents, and tricyclic antidepressants: Concomitant administration may increase the risk of cardiovascular adverse reactions. (7.5, 7.6)
- Monoamine-oxidase inhibitors: Concomitant administration may potentiate the effects and toxicity of monoamine-oxidase inhibitors. (7.7)

8 USE IN SPECIFIC POPULATIONS

- Lactation: Breastfeeding not recommended during treatment, but a lactating woman can pump and discard breast milk for 48 hours after treatment. (8.2)
- Geriatric Patients: May be more susceptible to cardiovascular adverse events. (8.5)
- Hepatic impairment: It is not recommended to dose NUMBRINO in patients with hepatic impairment. (8.6)
- Renal impairment: Monitor for adverse reactions such as headache, epistaxis, and clinically-relevant increases in heart rate or blood pressure. (8.7)
- Pseudocholinesterase deficiency. (8.8)

FULL PRESCRIBING INFORMATION

WARNING: ABUSE AND DEPENDENCE

CNS stimulants, including cocaine hydrochloride, have a high potential for abuse and dependence. (5.1)

1 INDICATIONS AND USAGE

NUMBRINO (cocaine hydrochloride) nasal solution is indicated for the induction of local anesthesia of the mucous membranes when performing diagnostic procedures and surgeries on or through the nasal cavities in adults.

2 DOSAGE AND ADMINISTRATION

2.1 Important Dosage and Administration Instructions

- NUMBRINO (cocaine hydrochloride) is for intranasal use only.
- Do not apply NUMBRINO to damaged nasal mucosa.
- Unless the FDA has determined that these products can be substituted, do not substitute NUMBRINO for other intranasal cocaine products because this may result in different local and/or systemic exposures.

2.2 Dosing Recommendations

The recommended dose of NUMBRINO ranges from 40 mg to 160 mg, depending on the nasal mucosal area to be anesthetized and the procedure to be performed. Each pledget absorbs one mL of NUMBRINO nasal solution. A maximum of two soaked cotton or rayon pledgets may be placed in each nasal cavity, for a total dose of 160 mg for NUMBRINO nasal solution 4%.

The total dose for any one procedure or surgery should not exceed 3 mg/kg cocaine hydrochloride.

The recommended size of the cotton or rayon pledgets for use with NUMBRINO measure ½ inch x 3 inch (sold separately).

2.3 Preparation and Administration of NUMBRINO via Pledgets

Draw up 4 mL NUMBRINO into a syringe calibrated in mL. Stack four pledgets and apply 2 mL of solution to the top of the stacked pledgets. Turn the stacked pledgets over and apply 2 mL of solution to the other side. NUMBRINO should be evenly distributed on all pledgets.

Following NUMBRINO application to pledgets, place One (1) or two (2) pledgets in each nasal cavity, for a maximum of 2 pledgets used per nostril.

Leave pledgets in place for up to 20 minutes. Remove pledgets and continue with the procedure. Discard pledgets, and dispose of any unused pledgets and remaining solution in accordance with institutional procedures for CII products.

Pledgets should be removed immediately upon any sign or symptom of an adverse event.

3 DOSAGE FORMS AND STRENGTHS

NUMBRINO (cocaine hydrochloride) nasal solution is a clear, blue-green solution provided in a concentration of 4% (40 mg/mL). The 4% nasal solution is provided in both a single-use 4 mL (160 mg/4 mL) and multiple-use 10 ml (400 mg/10 mL) bottles. Each 1 mL of the 4% solution contains 40 mg of cocaine hydrochloride, equivalent to 35.7 mg of cocaine free base as aqueous solution, for topical nasal administration.

4 CONTRAINDICATIONS

NUMBRINO is contraindicated in:

- patients with a known history of hypersensitivity to cocaine hydrochloride, other ester-based local anesthetics, or any other component of the nasal solution [see Warnings and Precautions (5.5)].

5 WARNINGS AND PRECAUTIONS

5.1 Potential for Abuse and Dependence

Central nervous system (CNS) stimulants, including cocaine hydrochloride, have a high potential for abuse and dependence [see Drug Abuse and Dependence (9.2, 9.3)].

5.2 Seizures

It has been reported in the literature that cocaine hydrochloride may lower the convulsive threshold. The risk may be higher in patients with a history of seizures or in patients with prior electroencephalogram (EEG) abnormalities without seizures, but has been reported in patients with no prior history or EEG evidence of seizures. Monitor patients for development of seizures.

5.3 Blood Pressure and Heart Rate Increases

As reported in the literature, cocaine hydrochloride causes an increase in observed blood pressure and heart rate. In the Phase 3 clinical studies with NUMBRINO, increases in blood pressure and heart rate were observed following pledget removal. Monitor for changes in vital signs, including heart rate and rhythm, after administration of NUMBRINO.

Avoid use of NUMBRINO in patients with a history of myocardial infarction, coronary artery disease, congestive heart failure, irregular heart rhythm, abnormal ECG, or uncontrolled hypertension. Avoid use of additional vasoconstrictor agents such as epinephrine or phenylephrine with NUMBRINO. If concomitant use is unavoidable, prolonged vital sign and ECG monitoring may be required.

Although not reported in the NUMBRINO clinical trials, myocardial infarction has been reported in the literature, and can occur when the drug has been used as recommended [see Adverse Reactions (6)].

5.4 Toxicology Screening

The time after cocaine administration for which cocaine and its metabolites can be detected in plasma and urine depends on the sensitivity of the utilized assay method. The cocaine hydrochloride and its metabolites in NUMBRINO may be detected in plasma for up to one week after administration. Cocaine hydrochloride and its metabolites may be detected in urine toxicology screening for longer than one week after administration.

5.5 Known Hypersensitivity or Idiosyncrasy to the Sympathomimetic Amines

NUMBRINO is contraindicated in patients with a known history of hypersensitivity to cocaine or to the components of the nasal solution. Cocaine is a sympathetic neuronal catecholamine reuptake inhibitor, which may potentiate the actions of concomitantly administered sympathomimetic amines.

5.6 Ophthalmic Use

NUMBRINO is NOT FOR OPHTHALMIC USE. Cocaine can cause sloughing of the corneal epithelium and should not be used in the eyes. Pitting and ulceration of the cornea has been reported in the literature.

6 ADVERSE REACTIONS

The following treatment-emergent adverse events are discussed in more detailed in other sections of the labeling:

- Increases in Blood Pressure and Heart Rate [see Warnings and Precautions (5.3)]

6.1 Clinical Trial Experience

Because clinical trials are conducted under widely varying conditions, adverse reaction rates observed in the clinical trials of a drug cannot be directly compared to rates in the clinical trials of another drug and may not reflect the rates observed in practice.

NUMBRINO nasal solution has been evaluated in one Phase 1 study, one QT study and two Phase 3 studies, which included 702 adult subjects who received a single application of NUMBRINO nasal solution 4%, NUMBRINO nasal solution 10%, or placebo. The randomized, double-blind, placebo controlled Phase 3 studies were conducted in adult patients undergoing diagnostic procedures and surgeries on or through the mucous membranes of the nasal cavities, of which 316 received NUMBRINO nasal solution 4%, 318 received NUMBRINO nasal solution 10%, and 168 received placebo. Safety was evaluated for up to 7 days after dosing.

In a Phase 3 study, patients received a mean dose of 126 mg (80 to 160 mg, N=259) of cocaine hydrochloride using NUMBRINO nasal solution 4% and a mean dose of 319 mg (200 to 400 mg, N=259) of cocaine hydrochloride using NUMBRINO nasal solution 10% as a single application.

The most common adverse reactions reported with NUMBRINO 4% are included in Table 1 (preexisting nasal conditions are not included). There were two patients treated with NUMBRINO nasal solution 4% who withdrew due to an adverse reaction. One patient developed anxiety and systolic hypertension and one patient developed intermittent paroxysmal tachycardia. Both patients developed symptoms within 10 minutes of nasal pledget application. Three patients treated with NUMBRINO nasal solution 10% required premature removal of pledgets due to nausea and diastolic hypertension; mild intermittent paroxysmal hypertension and paroxysmal tachycardia; and vasovagal syncope with bradycardia.

Table 1. Common Adverse Reactions with NUMBRINO in > 1% of Treated Patients

MedDRA System Organ Class and Preferred Term | NUMBRINO, 4%; (N=259) n, % | NUMBRINO, 10%; (N=259) n, % | Placebo; (N=128) n, %
Vascular Disorders | 203 (78) | 224 (87) | 86 (67)
Hypertension | 201 (78) | 220 (85) | 85 (66)
Cardiac Disorders | 31 (12) | 47 (18) | 10 (8)
Tachycardia | 12 (5) | 28 (11) | 1 (1)
Bradycardia | 8 (3) | 1 (0.4) | 5 (4)
Sinus tachycardia | 6 (2) | 9 (4) | 0
Investigations | 13 (5) | 30 (12) | 8 (6)
QRS prolonged | 4 (2) | 8 (3) | 3 (2)
QT interval prolonged | 7 (3) | 10 (4) | 3 (2)

6.2 Postmarketing Experience

The following adverse reactions have been identified during use of Cocaine Hydrochloride Nasal Solution. Because these reactions are reported voluntarily from a population of uncertain size, it is not always possible to reliably estimate their frequency or establish a causal relationship to drug exposure.

Nervous system disorders: Headache, Seizure

Cardiac disorders: Hypertension, tachycardia, atrial and ventricular arrhythmias, myocardial ischemia and infarction

Psychiatric disorders: Anxiety

7 DRUG INTERACTIONS

7.1 Central Nervous System Stimulants

Concurrent use of other central nervous system stimulants with cocaine may result in excessive stimulation, leading to nervousness, irritability, or possibly convulsions, or cardiac arrhythmias.

7.2 Epinephrine, Phenylephrine

There are reports in the published literature of myocardial ischemia, myocardial infarction, and ventricular arrhythmias after concomitant administration of topical intranasal cocaine with epinephrine and phenylephrine during nasal and sinus surgery.

Avoid use of additional vasoconstrictor agents such as epinephrine and phenylephrine with NUMBRINO during nasal and sinus surgery. If concomitant use is unavoidable, prolonged vital sign and ECG monitoring may be required.

7.3 Disulfiram

Published literature reported that disulfiram treatment increased plasma cocaine exposure (AUC and Cmax), by several folds after acute intranasal cocaine administration. Another literature reported that co-administration of disulfiram increased AUC of plasma cocaine by several folds after intravenous cocaine administration [see Clinical Pharmacology (12.3)].

Avoid using NUMBRINO in patients taking disulfiram. Consider using other local anesthesia.

7.4 Cholinesterase Inhibitors

Cocaine has been described in literature to be primarily metabolized and inactivated by non-enzymatic ester hydrolysis and hepatic carboxylesterase, and also by plasma cholinesterase, hepatic carboxylesterase, and CYP3A4. The pharmacokinetics of NUMBRINO in patients with reduced plasma cholinesterase activity has not been studied.

Plasma cholinesterase activity may be decreased by chronic administration of certain monoamine oxidase inhibitors, oral contraceptives, glucocorticoids, antimyasthenics (neostigmine), cyclophosphamide, and possibly thiotepa.

It may also be diminished by administration of irreversible plasma cholinesterase inhibitors such as echothiophate, organophosphate insecticides, and certain antineoplastic agents. Patients with reduced plasma cholinesterase (pseudocholinesterase) activity may have reduced clearance and increased exposure of plasma cocaine after administration of NUMBRINO.

Because cocaine is metabolized by multiple enzymes, the effect of reduced plasma cholinesterase activity on cocaine exposure may be limited. No dosage adjustment of NUMBRINO is needed in patients with reduced plasma cholinesterase. Monitor patients with reduced plasma cholinesterase activity for adverse reactions such as clinically-relevant increases in heart rate or blood pressure.

7.5 Postganglionic Blocking Agents

Agents such as reserpine potentiate cocaine-induced sympathetic stimulation; concurrent use may increase the risk of hypertension and cardiac arrhythmias that may be life-threatening.

7.6 Tricyclic Antidepressants

Tricyclic antidepressants may increase the activity of the sympathetic nervous system, which may also be increased by administration of cocaine hydrochloride.

7.7 Monoamine-Oxidase Inhibitors

Cocaine hydrochloride may potentiate the effects and toxicity of MAO inhibitors.

8 USE IN SPECIFIC POPULATIONS

8.1 Pregnancy

Risk Summary

There are no available data on the use of NUMBRINO in pregnant women to identify a drug-associated risk of major birth defects, miscarriage or adverse maternal or fetal outcomes. Adverse maternal and fetal/neonatal outcomes have been seen in women with chronic cocaine abuse during pregnancy (see Data).

In published animal reproduction studies, cocaine administered to pregnant females during the gestational period produced hydronephrosis (0.5 times the human reference dose (HRD) of 37.5 mg via the 4% solution), developmental delays in the offspring (1.5 times the HRD), cerebral hemorrhage and fetal edema (2.0 times the HRD), reduced fetal body weights and brain weights (2.6 times the HRD), and reduced fetal survival (3.7 times the HRD).

Single dose administration of cocaine intravenously during organogenesis in mice produced cryptochidism, anophthalmia, exencephaly, and delayed ossification at 7.8 times the HRD. In rats, a single dose of cocaine administered by intraperitoneal injection produced edematous fetuses, hemorrhages and limb defects at 12.9 times the HRD (see Data).

The estimated background risk of major birth defects and miscarriage for the indicated population(s) are unknown. All pregnancies have a background risk of birth defect, loss, or other adverse outcomes. In the U.S. general population, the estimated background risk of major birth defects and miscarriage in clinically recognized pregnancies is 2-4% and 15-20%, respectively.

Data

Human Data

There are no available data on the use of intranasal cocaine hydrochloride solution in pregnant women to inform a drug-associated risk for major congenital malformations or miscarriage. There are published data describing adverse developmental outcomes in women with chronic cocaine abuse during pregnancy. The published case-control and observational studies examining the effect of in utero cocaine exposure on fetal growth parameters, after controlling for confounding variables, found exposure was associated with reduced fetal growth compared with non-drug-abuse populations.

Published data from a large number of studies of women with chronic cocaine abuse during pregnancy are inconsistent in their findings with regard to congenital malformations, prematurity, miscarriage, premature rupture of membranes and gestational hypertension. The applicability of the findings from these studies of chronic abuse in pregnancy to a single topical exposure is limited.

Animal Data

Formal animal reproduction and development studies have not been conducted with intranasal cocaine hydrochloride. However, reproduction and development studies with cocaine have been reported in the published literature. Exposure margins below are based on body surface area comparison to the human reference dose (HRD) of 37.5 mg (estimated amount absorbed from the 160 mg (4%) cocaine-soaked pledgets).

Hydronephrosis was noted in embryos from pregnant rats treated wtih cocaine 2.1 mg/kg (0.5 times the HRD) and higher from Gestation Day 0 to 9. Cerebral hemorrhage and endematous fetuses were noted at 2.2 times the HRD and above).

Developmental delays and altered spontaneous exploratory behavior in response to cocaine were reported in rat pups born to dams treated intravenously with 6 mg/kg cocaine (1.5 times the HRD) from Gestation Day 8 to 20 in the absence of maternal toxicity.

Reduced fetal body and brain weights and alterations in fetal central neurotransmitter levels were noted following treatment of pregnant mice with 20 mg/kg cocaine from gestation days 8 to 12 or 12 to 18 (2.6 times the HRD).

Reduced fetal survival was noted when pregnant nonhuman primates were dosed with 0.3 mg/kg/h cocaine (3.7 times the HRD on per day basis) via a subcutaneous minipump from Gestation Day 24 to birth.

Exencephaly, cryptochidism, hydronephrosis, anophthalmia, delayed ossification, limb anomalies, and cerebral and intra-abdominal hemorrhage were reported following a single subcutaneous injection of 60 mg/kg cocaine (7.8 times the HRD) to pregant mice between Gestation Day 7 to 12. No significant maternal toxicity was reported at this dose.

Deficits in associational learning were reported when pregnant rats were treated with cocaine during gestation (10.3 times the HRD) in the absence of maternal toxicity.

Hemorrhage, fetal edema, and limb defects were reported when pregnant rats were administered a single injection of cocaine at a dose of 50 mg/kg/day or higher (12.9 times the HRD) during Gestation Day 9 to 19. Increased resorptions were noted at doses higher than 70 mg/kg/day (18.1 times the HRD) when administered on Gestation Day 16. No adverse effects were reported at a dose of 40 mg/kg (10.3 times the HRD).

Fetal deaths, decreased fetal body weights, edematous fetuses and single incidences of cleft palate and hypertrophic ventricle were observed when pregnant rats were treated with intraperitoneal cocaine at 60 mg/kg (15.5 times the HRD) from Gestation Day 8 to 12. Maternal toxicity was noted at this dose (mortality). No adverse effect level for fetal and maternal toxicity was noted at 50 mg/kg/day (13 times the HRD).

Decreased body weights, overall body length and crown circumference of offspring were reported when pregnant Rhesus monkeys were treated with escalating doses up to 7.5 mg/kg cocaine TID intramuscularly per day for 5 days per week from prior to conception to term (11.6 times the HRD).

8.2 Lactation

Risk Summary

Based on case reports in published literature, cocaine is present in human milk at widely varying concentrations. Based on its pharmacochemical characteristics, high concentrations of cocaine are expected in breast milk with systemic exposure. The applicability of these findings to a single topical exposure with limited systemic absorption is unclear. No studies have evaluated cocaine concentrations in milk after topical administration of NUMBRINO.

Cocaine is detected in human breastmilk in chronic abuse situations and is expected to be at higher concentrations in milk than in maternal blood based on its physicochemical characteristics. Breastfeeding immediately after administration of NUMBRINO could result in infant plasma concentrations that are approximately half the anticipated maximum maternal plasma concentrations at the clinical dose of 160 mg. The effects of this cocaine plasma concentration in an infant are unknown, but no level of cocaine exposure is considered safe for a breastfed infant.

Adverse reactions have occurred in infants ingesting cocaine through breastmilk, including vomiting, diarrhea, convulsions, hypertension, tachycardia, agitation and irritability. The long-term effects on infants exposed to cocaine through breast milk are unknown. There are no data on the effects of NUMBRINO on milk production.

Because of the potential for serious adverse reactions in breastfed infants, advise a lactating woman that breastfeeding is not recommended during treatment with NUMBRINO and to pump and discard breastmilk for 48 hours after use of NUMBRINO.

8.3 Females and Males of Reproductive Potential

Published animal studies suggest that cocaine can alter female reproductive hormone levels, disrupt the estrous cycle, and reduce ovulation at doses approximately 1 to 2 times the HRD based on body surface area [see Nonclinical Toxicology (13.1)].

8.4 Pediatric Use

Safety and effectiveness of NUMBRINO in pediatric patients under the age of 18 have not been established.

Published studies state that in juvenile male rats, 30 mg/kg subcutaneous cocaine administration for longer than 7 days (7.8 times the HRD) produced testicular necrosis. Treatment of juvenile male rats with 15 mg/kg (3.9 times the HRD) for 100 days resulted in abnormal sperm morphology and reduced pregnancy rates.

8.5 Geriatric Use

Of the 802 subjects in the two Phase 3 studies with NUMBRINO 13 subjects (1.6%) were age 65 and older, and one subject (0.1%) was 75 years of age or older.

No untoward or unexpected adverse reactions were seen in elderly patients who received NUMBRINO compared to those subjects that were under the age of 65.

However, hypertension was observed in all geriatric subjects receiving NUMBRINO. Special precaution should be given when determining the dose of NUMBRINO for geriatric patients, commensurate with their age and physical status.

8.6 Hepatic Impairment

According to literature, cocaine is eliminated predominantly by metabolism in humans. The clearance of NUMBRINO 4% has not been evaluated in subjects with hepatic impairment when compared to patients with normal hepatic function, and sufficient data are not available in literature to guide dosing in these subjects. Thus, NUMBRINO should be avoided in patients with hepatic impairment [see Clinical Pharmacology (12.3)].

8.7 Renal Impairment

According to literature, cocaine is eliminated predominantly by metabolism in humans, with little excreted unchanged in the urine. The pharmacokinetics of NUMBRINO in patients with renal impairment has not been studied. Based on information available on the metabolism and excretion of cocaine, dose initiation in patients with renal impairment should follow a conservative approach. Monitor patients with renal impairment for adverse reactions such as clinically-relevant increases in heart rate or blood pressure [see Clinical Pharmacology (12.3)].

8.8 Pseudocholinesterase Deficiency

Pharmacokinetics of NUMBRINO in patients with reduced plasma cholinesterase activity has not been studied.

Genetic abnormalities of plasma cholinesterase (e.g., patients who are heterozygous or homozygous for atypical plasma cholinesterase gene), disease conditions such as malignant tumors, severe liver or kidney disease, decompensated heart disease, infections, burns, anemia, peptic ulcer, or myxedema or other physiological states such as pregnancy may lead to reduced plasma cholinesterase activity. Patients with reduced plasma cholinesterase (pseudocholinesterase) activity may have reduced clearance and increased exposure of plasma cocaine after administration of NUMBRINO.

Because cocaine is metabolized by multiple enzymes, the effect of reduced plasma cholinesterase activity on cocaine exposure may be limited. No dosage adjustment of NUMBRINO is needed in patients with reduced plasma cholinesterase. Monitor patients with reduced plasma cholinesterase activity for adverse reactions such as, clinically-relevant increases in heart rate or blood pressure [see Contraindications (4)].

9 DRUG ABUSE AND DEPENDENCE

9.1 Controlled Substance

NUMBRINO contains cocaine, a Schedule II controlled substance.

9.2 Abuse

NUMBRINO contains cocaine, a substance with a high potential for abuse. NUMBRINO can be misused and abused, which can lead to addiction. NUMBRINO may also be diverted for abuse purposes [see Warnings and Precautions (5.1)].

Drug abuse is the intentional non-therapeutic use of a prescription drug, even once, for its rewarding psychological or physiological effects. Drug addiction is a cluster of behavioral, cognitive, and physiological phenomena that develop after repeated substance use and includes: a strong desire to take the drug, difficulties in controlling its use, persisting in its use despite harmful consequences, a higher priority given to drug use than to other activities and obligations, increased tolerance, and sometimes a physical withdrawal. Drug abuse of a substance may occur without progression to drug addiction. “Drug-seeking” behavior is very common in persons with substance use disorders.

Drug abuse and addiction are conditions that are separate and distinct from physical dependence and tolerance [see Dependence (9.3)]. Health care providers should be aware that abuse and addiction may occur in the absence of symptoms indicative of physical dependence and tolerance.

Individuals who abuse stimulants may use NUMBRINO for abuse purposes. Adverse events associated with abuse of cocaine include euphoria, excitation, irritability, restlessness, anxiety, paranoia, confusion, headache, psychosis, hypertension, stroke, seizures, dilated pupils, nausea, vomiting, and abdominal pain. Intranasal abuse can produce damage to the nostrils (e.g., ulceration and deviated septum). Abuse of cocaine can result in overdose, convulsions, unconsciousness, coma, and death [see Overdosage (10)].

NUMBRINO, like all prescription drugs with abuse potential, can be diverted for non-medical use into illicit channels of distribution. In order to minimize these risks, effective accounting procedures should be implemented, in addition to routine procedures for handling controlled substances.

9.3 Dependence

Physical dependence is a state that develops as a result of physiological adaptation in response to repeated drug use, manifested by withdrawal signs and symptoms after abrupt discontinuation or a significant dose reduction of a drug. NUMBRINO is approved for nasal single use, so physical dependence and withdrawal symptoms are unlikely to develop. Although NUMBRINO is not indicated for chronic therapy, repeated misuse or abuse of this product may lead to physical dependence.

10 OVERDOSAGE

No cases of overdose with NUMBRINO were reported in clinical trials. Reported blood pressure and heart rate increases were greater with NUMBRINO nasal solution 10% than with NUMBRINO nasal solution 4%.

In the case of an overdose, consult with a Certified Poison Control Center (1-800-222-1222) for up-to-date guidance and advice for treatment of overdosage. Individual patient response to cocaine varies widely. Toxic symptoms may occur idiosyncratically at low doses.

Manifestations of cocaine overdose associated with illicit use of cocaine reported in literature and based on reports in FDA’s Adverse Events Reporting System (AERS) database include death, cardio-respiratory arrest, cardiac arrest, respiratory arrest, tachycardia, myocardial infarction, agitation, aggression, restlessness, tremor, hyperreflexia, rapid respiration, confusion, assaultiveness, hallucinations, panic states, hyperpyrexia, and rhabdomyolysis. Fatigue and depression usually follow the central nervous system stimulation. Other reactions include arrhythmias, hypertension or hypotension, circulatory collapse, nausea, vomiting, diarrhea, and abdominal cramps. Fatal poisoning is usually preceded by convulsions and coma.

Because cocaine is significantly distributed to tissues and rapidly metabolized, dialysis and hemoperfusion are not effective. Acidification of the urine does not significantly enhance cocaine elimination.

11 DESCRIPTION

NUMBRINOTM (cocaine hydrochloride) nasal solution is a clear, blue-green, aqueous solution, available in 4% strength. Each 1 mL contains cocaine hydrochloride 40 mg, equivalent to 35.7 mg of cocaine free base; 4% as 160 mg/4 mL or 400 mg/10 mL.

Cocaine, (1R,2R,3S,5S) methyl 3-(benzoyloxy)-8-methyl-8-azabicyclo[3.2.1]octane-2-carboxylate hydrochloride, is a synthetic tropane alkaloid ester, local anesthetic, which occurs as colorless to white crystals or white crystalline powder.

The structural formula for cocaine hydrochloride is as follows:

Formula C17H21NO4 HCl Molecular weight 339.81

NUMBRINO also contains the following inactive ingredients: purified water, citric acid (anhydrous), sodium benzoate, D&C Yellow No. 10, and FD&C Green No. 3.

12 CLINICAL PHARMACOLOGY

12.1 Mechanism of Action

Cocaine hydrochloride is a local anesthetic of the ester type. Cocaine hydrochloride prevents conduction in nerve fibers by reversibly blocking voltage-gated sodium channels and preventing the transient rise in sodium conductance necessary for generation of an action potential.

12.2 Pharmacodynamics

Cardiac Electrophysiology

The effect of cocaine hydrochloride topical solution on the QTc interval was evaluated in a randomized, positive- and placebo-controlled four-period crossover thorough QTc study in 32 healthy subjects. NUMBRINO is associated with concentration-dependent QTc prolongation. Based on the concentration-QTc relationship, the mean placebo corrected change from the baseline QTcF (90% two-sided upper confidence interval) are 4.7 ms (6.2 ms) and 15.4 ms (20.1 ms) at peak concentrations of 143 ng/mL (corresponds to 4% single dose, 160 mg) and 434 ng/mL (corresponds to 10% single dose, 400 mg), respectively. The estimates of the QTcF interval are confounded by increased heart rates. The QTc prolongation observed with NUMBRINO (4% single dose) was found to be below the regulatory threshold for concern.

NUMBRINO is associated with increases in heart rate. The mean placebo corrected change from baseline heart rate (90% two-sided upper confidence interval) are 12 (14) bpm and 20 (22) bpm for the 4% and 10%, respectively.

Effects on Cardiovascular System

Cocaine can potentiate central and peripheral sympathetic effects on the cardiovascular system, resulting in increased inotropic and chronotropic effects, increased cardiac activity, and tachycardia. Intense peripheral vasoconstriction may result in elevated systolic and diastolic blood pressure.

Effects on Vascular System

The relationship between local anesthetic effectiveness and toxicity of cocaine is a function of the patient’s state of health, medical condition, nasal mucosa integrity and extent of systemic absorption of cocaine (from the pledgets). When applied to mucous membranes by pledget administration, topical anesthesia develops rapidly and persists for 30 minutes or longer depending on the concentration of cocaine hydrochloride solution used, the dose, and on the vascularity of the tissue.

12.3 Pharmacokinetics

NUMBRINO is an aqueous solution of cocaine hydrochloride for topical use only.

Absorption

Application of NUMBRINO for 20 minutes by pledget administration to the nasal mucosa in healthy adults may reduce the systemic absorption of the applied dose of cocaine hydrochloride compared to the systemic absorption after non-pledget administration. The estimated mean systemic absorption of cocaine from a single 160 mg dose (4 mL, 4%) was 23.44% of the topically applied dose. (Table 2).

Table 2. Systemic Absorption of NUMBRINO in Healthy Adult Subjects Minimized by Pledget Administration (single nasal dose of 160 mg Cocaine Hydrochloride Topical Solution over 20 minutes)

NUMBRINO; Dose (4 mL) | Age Range (yr) | Application Time; (min) | Estimated^1 Systemic Absorption | Mean Cmax; (ng/mL) | Median; Tmax (min); Cmax (ng/mL)
160 mg (4%) | 20-40 | 20 | 23.44% | 142.68; n=33 | 30; 142.7
^1Estimated absorbed dose was calculated by subtracting the residual amount of drug in the pledgets from the administered dose; Tmax includes time 0 (the start of pledget insertion to pledget removal (20 minutes) to the time Cmax was observed, i.e. 10 minutes after removal of the pledgets.

Distribution

Cocaine has been described in literature as approximately 84-92% bound to human plasma proteins. Cocaine is extensively distributed to tissues and crosses the blood brain barrier. Its volume of distribution is approximately 2 L/kg. Cocaine crosses the placenta by simple diffusion and accumulates in the fetus after repeated use.

Elimination

Metabolism

Cocaine is metabolized by two major hydrolytic pathways. Cocaine is metabolized by hydrolysis to benzoylecgonine (major, but inactive metabolite) by hepatic carboxylesterase-1. Cocaine is also metabolized by hydrolysis to ecgonine methyl ester (major, but inactive metabolite) by plasma butyrylcholinesterase and hepatic carboxylesterase-2.

Cocaine is minimally metabolized by hydrolysis to ecgonine (minor, inactive metabolite) by carboxylesterase-2.

Cocaine is N-demethylated by the CYP3A4 enzyme system to produce the active metabolite, norcocaine. Total systemic exposure of norcocaine is less than one percent that observed with cocaine.

Excretion

Cocaine is excreted almost exclusively in the urine, as metabolites. Only a minor fraction of cocaine is eliminated unchanged in the urine (<5%).

The apparent elimination half-life of cocaine following administration of NUMBRINO (by pledgets) was 1.54 hours) for the 4% concentration.

Specific Populations

Geriatric Patients

The pharmacokinetics of NUMBRINO in patients over the age of 65 has not of been studied.

Patients with Hepatic Impairment

The pharmacokinetics of NUMBRINO in patients with hepatic impairment has not been studied.

Patients with Renal Impairment

The pharmacokinetics of NUMBRINO in patients with renal impairment has not been studied.

Drug-drug Interactions:

Disulfiram

It has been reported in the published literature that disulfiram treatment increased plasma cocaine exposure, including both AUC and Cmax, by several folds after acute intranasal cocaine administration. Another published literature reported that co-administration of disulfiram increased AUC of plasma cocaine by several folds after intravenous cocaine administration [see Drug Interactions (7.1)].

13 NONCLINICAL TOXICOLOGY

13.1 Carcinogenesis, Mutagenesis, Impairment of Fertility

Carcinogenesis

Long-term studies in animals have not been performed to evaluate the carcinogenic potential of cocaine.

Mutagenesis

Cocaine hydrochloride was not mutagenic in an in vitro bacterial reverse mutation assay (Ames test) and was not clastogenic in an in vitro chromosomal aberrations assay or in the in vivo rat micronucleus test.

Impairment of Fertility

Studies in animals to characterize the effects of cocaine on fertility have not been completed. There are published studies that provide some information on the potential impact of cocaine on fertility. Exposure margins below are based on body surface area comparison to the human reference dose (HRD) of 37.5 mg (estimated amount absorbed from the 160 mg cocaine-soaked pledgets).

Suppression of estrous/menstrual cyclicity and ovulation was reported 1.3 to 2.6 times and 2 times the HRD in rats and monkeys, respectively.

In a published study in older male rats (16 weeks) 30 mg/kg cocaine SC (7.8 times the HRD) for 72 days prior to mating did not alter male fertility or alter male reproductive tissue histopathology but did increase the incidence of abnormal sperm and resulted in hyperactivity of next generation offspring.

14 CLINICAL STUDIES

Efficacy was demonstrated in one multicenter, randomized, double-blind, placebo-controlled, parallel-arm, clinical trial comparing a single-dose of 4% and 10% NUMBRINO and placebo applied to pledgets and delivered to the nasal mucosa in patients requiring a diagnostic or surgical procedure on or through accessible mucous membranes of the nasal cavities. One trial was terminated early in order to update the trial to refine its operation.

The primary endpoint was nasal anesthetic success, defined as immediate anesthesia based on a numeric pain rating score (NPRS) of 0 (no pain, 0 to 10 scale) 20 minutes post-application of the nasal cavity pledget dose, and sustained anesthesia based on the lack of need for additional anesthesia or analgesics for the remainder of the diagnostic procedure or surgery.

Study drug was applied to the nasal mucosa for 20 minutes via cotton or rayon pledgets, measuring 0.5 inches by 3 inches. The most commonly performed procedures included nasal endoscopy (62%) and transnasal laryngoscopy (24%). Less frequently performed procedures included sinus endoscopy (6%), nasal biopsy (0.25%), and turbinate reduction (0.25%).

Nasal anesthesia was assessed using the visual numeric rating scale (VNRS) during a von Frey monofilament test prior to the diagnostic procedure or surgery. After subject-reported pain scores were collected, the blind to placebo was broken and placebo patients did not undergo a study procedure or surgery. Cocaine patients who reported a pain score of 0 proceeded to the scheduled procedure.

A total of 639 patients were randomized and received a single application of either cocaine hydrochloride nasal solution, 4% (n=258), cocaine hydrochloride nasal solution, 10% (n=254), or placebo (n=127). Sixty-one percent (61%) of randomized patients were female and 81% were white, with a mean age of 38 years (range 18 to 76 years). Patients with a history of myocardial infarction, coronary artery disease, congestive heart failure, irregular heart rhythm, abnormal screening ECG, or uncontrolled hypertension, defined as systolic blood pressure ≥140 mmHg or diastolic blood pressure ≥90 mmHg, were excluded from participating in the study.

The efficacy endpoint was anesthetic success, defined as immediate anesthesia based on a score of 0 on a NPRS during a von Frey monofilament test 20 minutes after study drug administration, and sustained anesthesia throughout the diagnostic procedure or surgery based on no further anesthetic or analgesic treatment required.

Efficacy Results

Table 3 provides results for anesthetic success rate by treatment group.

Table 3: Anesthetic Success

Event | Placebo (N=127) | Cocaine 4% (N=258) | Cocaine 10% (N=254)
Success | 25 (20%) | 183 (71%) | 210 (83%)
Failure | 102 (80%) | 75 (29%) | 44 (17%)

Of the 75 (29%) failures in the cocaine hydrochloride 4% group, 2 patients requested additional anesthetic medication. Of the 44 (17%) failures in the cocaine 10% group, 1 patient requested additional anesthetic medication.

16 HOW SUPPLIED/STORAGE AND HANDLING

16.1 How Supplied

NUMBRINOTM (cocaine hydrochloride) nasal solution is a clear, blue-green solution available as follows:

4% (40 mg/ mL) Nasal Solution

NDC 81665-300-02: 4mL Single-use Bottles
NDC 81665-300-03: 10mL Multi-use Bottles

16.2 Storage and Handling

Store at 20° to 25°C (68° to 77°F) with excursions permitted between 15° and 30°C (59° and 86° F) [see USP Controlled Room Temperature].

17 PATIENT COUNSELING INFORMATION

Pregnancy

Inform female patients of reproductive potential that NUMBRINO may cause fetal harm and to inform their prescriber of a known or suspected pregnancy [see Use in Specific Populations (8.1)].

Lactation

Advise a woman that breastfeeding is not recommended during treatment with NUMBRINO and to pump and discard breastmilk for 48 hours after administration of NUMBRINO [see Use in Specific Populations (8.2)].

Blood Pressure and Heart Rate Increase

Advise patients that NUMBRINO can cause increases in blood pressure and heart rate. Instruct patients to contact their health care professional if these symptoms persist [see Warnings and Precautions (5.3)].

Seizures

Advise patients that NUMBRINO may lower the seizure threshold. Patients should be monitored for the development of seizures [see Warnings and Precautions (5.2)].

Toxicology Screening

The time after cocaine administration for which cocaine and its metabolites can be detected in plasma and urine depends on the sensitivity of the utilized assay method. Advise patients that cocaine hydrochloride and its metabolites in NUMBRINO may be detected in plasma for up to one week after administration. Cocaine hydrochloride and its metabolites may be detected in urine toxicology screening for longer than one week after administration [see Warnings and Precautions (5.4)].

Concomitant CNS Stimulants

Advise patients to inform their health care professional if they are taking CNS stimulants, alpha-modifying agents, monoamine oxidase inhibitors, or tricyclic antidepressants [see Drug Interactions (7.1)].

Hypersensitivity Reactions

Advise patients of the signs and symptoms of hypersensitivity reactions and to seek immediate medical attention should they occur [see Warnings and Precautions (5.5)].

Distributed by:
Omnivium Pharmaceuticals
Rahway, NJ 07065

Rev. 08/2023
CIB72177A

4% 4 mL Vial Label

NDC 81665-300-02

single-use 4 mL

NUMBRINOTM

(cocaine hydrochloride*) CII
nasal solution

4% (40 mg/mL)

(*equivalent to 35.7 mg cocaine base)

FOR TOPICAL USE ONLY.
NOT FOR INJECTION OR
OPHTHALMIC USE

Rx Only

Omnivium Pharmaceuticals

4% 4 mL Carton

NDC 81665-300-02

single-use 4 mL

NUMBRINOTM

(cocaine hydrochloride*) CII
nasal solution
4% (40 mg/mL)

(*equivalent to 35.7 mg cocaine base)

FOR TOPICAL USE ONLY.
NOT FOR INJECTION OR
OPHTHALMIC USE

Rx Only

Omnivium Pharmaceuticals